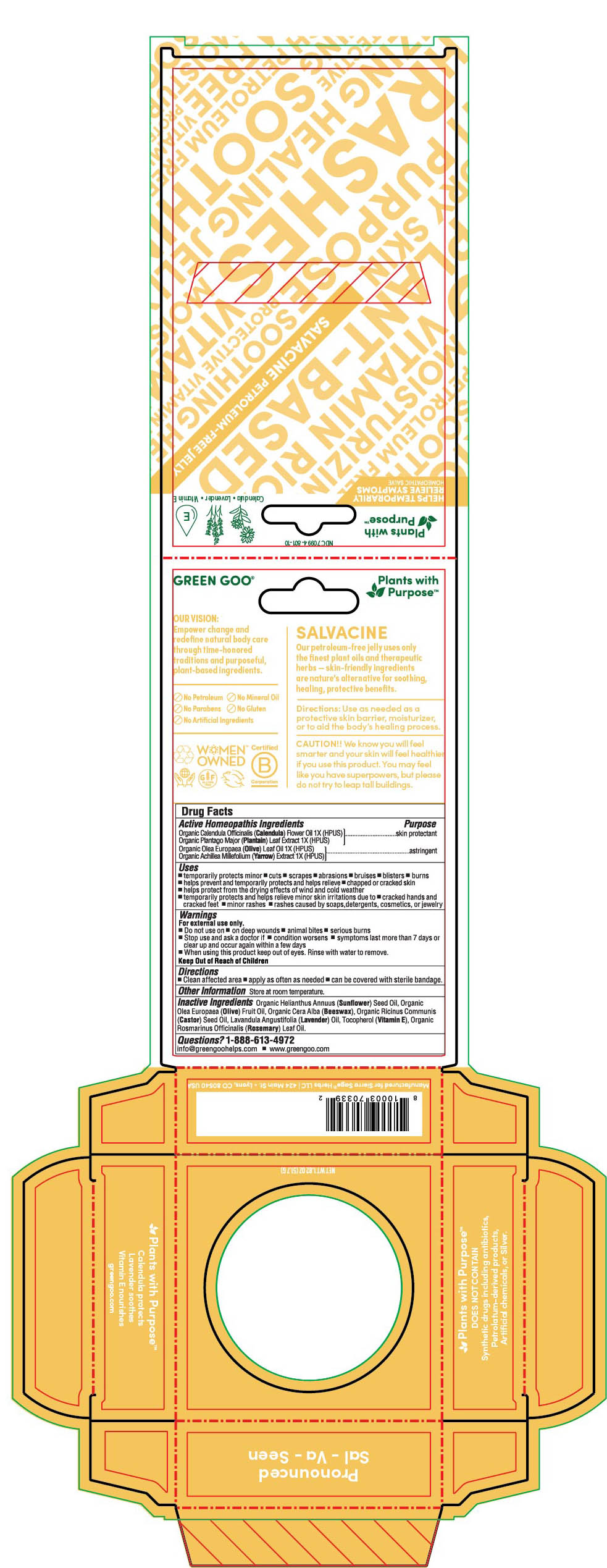 DRUG LABEL: Salvacine
NDC: 70994-801 | Form: SALVE
Manufacturer: Spry Life LLC
Category: homeopathic | Type: HUMAN OTC DRUG LABEL
Date: 20251215

ACTIVE INGREDIENTS: OLEA EUROPAEA LEAF 1 [hp_X]/100 g; ACHILLEA MILLEFOLIUM FLOWER 1 [hp_X]/100 g; CALENDULA OFFICINALIS FLOWER 1 [hp_X]/100 g; PLANTAGO MAJOR 1 [hp_X]/100 g
INACTIVE INGREDIENTS: YELLOW WAX; ALPHA-TOCOPHEROL; ROSEMARY OIL; LAVENDER OIL; OLIVE OIL; SUNFLOWER OIL; CASTOR OIL

Salvacine Homeopathic Salve

Purpose Section

Skin Protectant

Astringent

Active Ingredients

Organic Calendula Officinalis (Calendula) Flower Oil 1X (HPUS)
Organic Plantago Major (Plantain) Leaf Extract 1X (HPUS)

Organic Olea Europaea (Olive) Leaf Oil 1X (HPUS)

OrganicAchilleaMillefolium(Yarrow)Extract1X(HPUS)

Indications & Usage

• temporarily protects minor • cuts • scrapes • abrasions • bruises • blisters • burns

▪︎ temporarily protects and helps relieve • chapped or cracked skin

▪︎ helps protect from the drying effects of wind and cold weather
▪︎ temporarily protects and helps relieve minor skin irritations and itching due to • cracked hands and cracked feet • minor rashes • rashes caused by soaps, detergents, cosmetics, or jewelry

Keep out of reach of children section

Keep out of reach of children.

Warnings Section

Warnings

For external use only.

• Do not use on • deep wounds • animal bites • serious burns

• Stop use and ask a doctor if • condition worsens • symptoms last more than 7 days or clear up and occur again within a few days

• When using this product keep out of eyes. Rinse with water to remove.

Storage

Store at room temperature.

Dosage & Administration Section

• clean affected area • Apply as often as needed • can be covered with strile bandage

Inactive Ingredients

Organic Helianthus Annuus (Sunflower) Seed Oil, Organic Olea Europaea (Olive) Fruit Oil, Organic Cera Alba (Beeswax), Organic Ricinus Communis (Castor) Seed Oil, Lavandula Angustifolia (Lavender) Oil, Tocopherol (Vitamin E), Rosmarinus Officinalis (Rosemary) Leaf Oil.